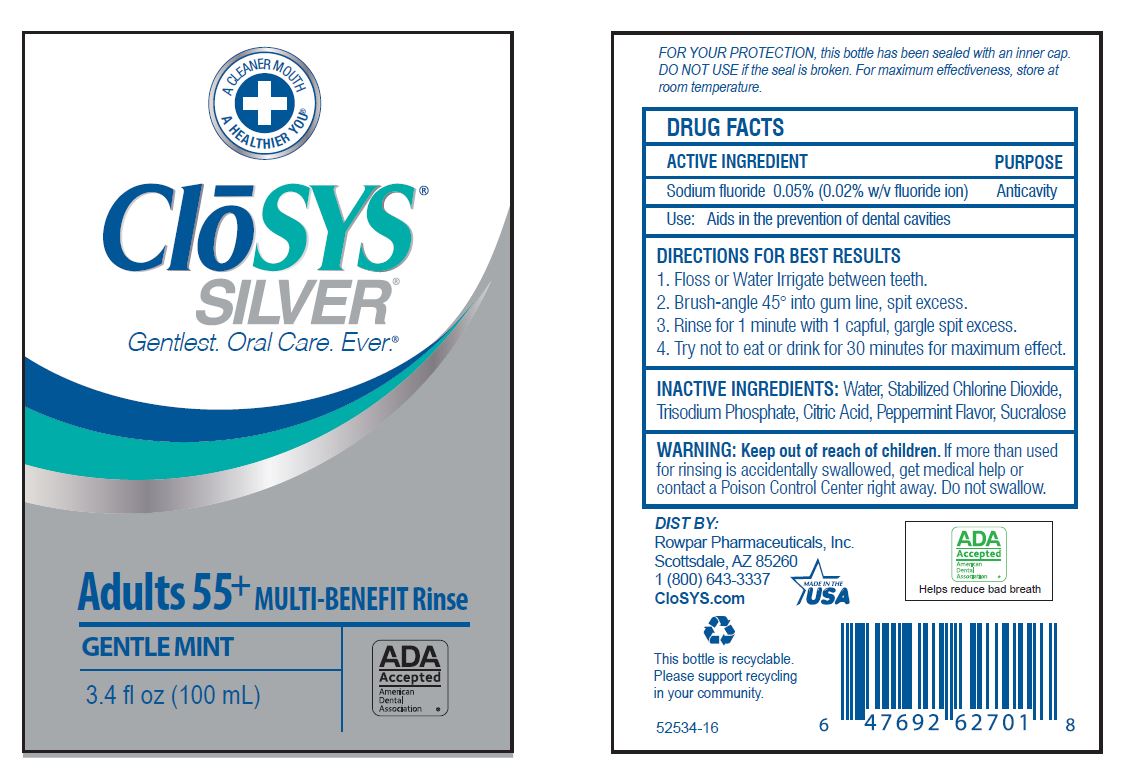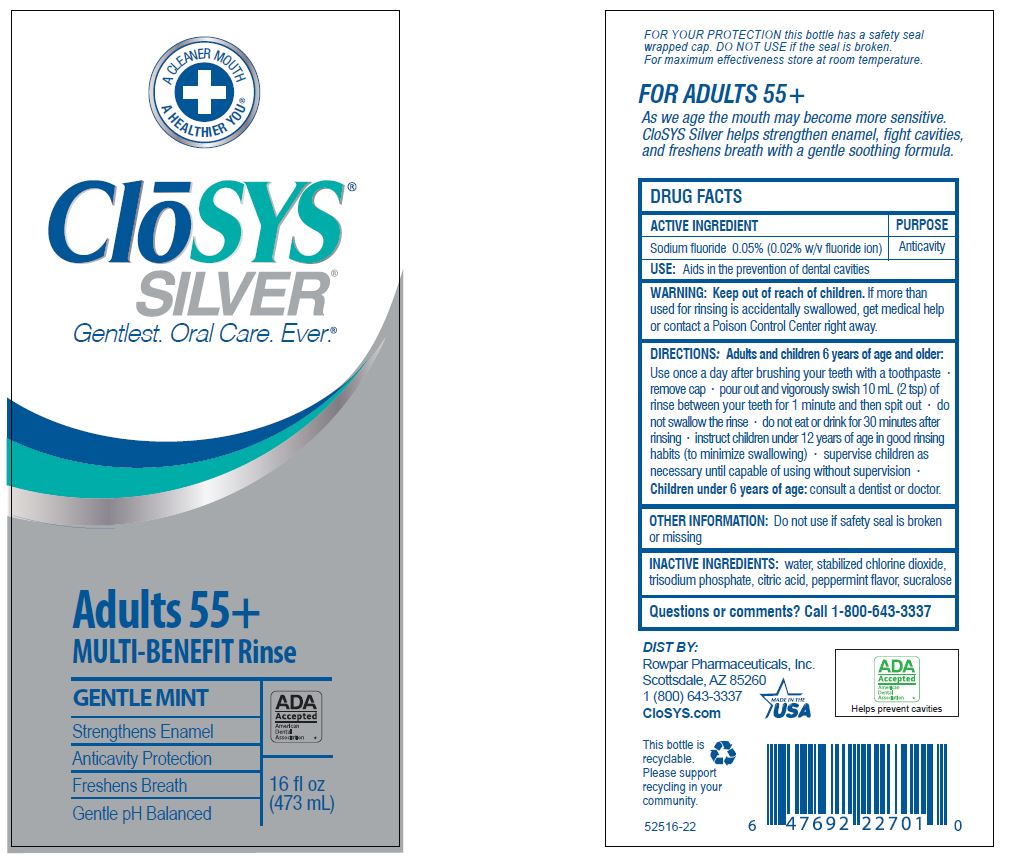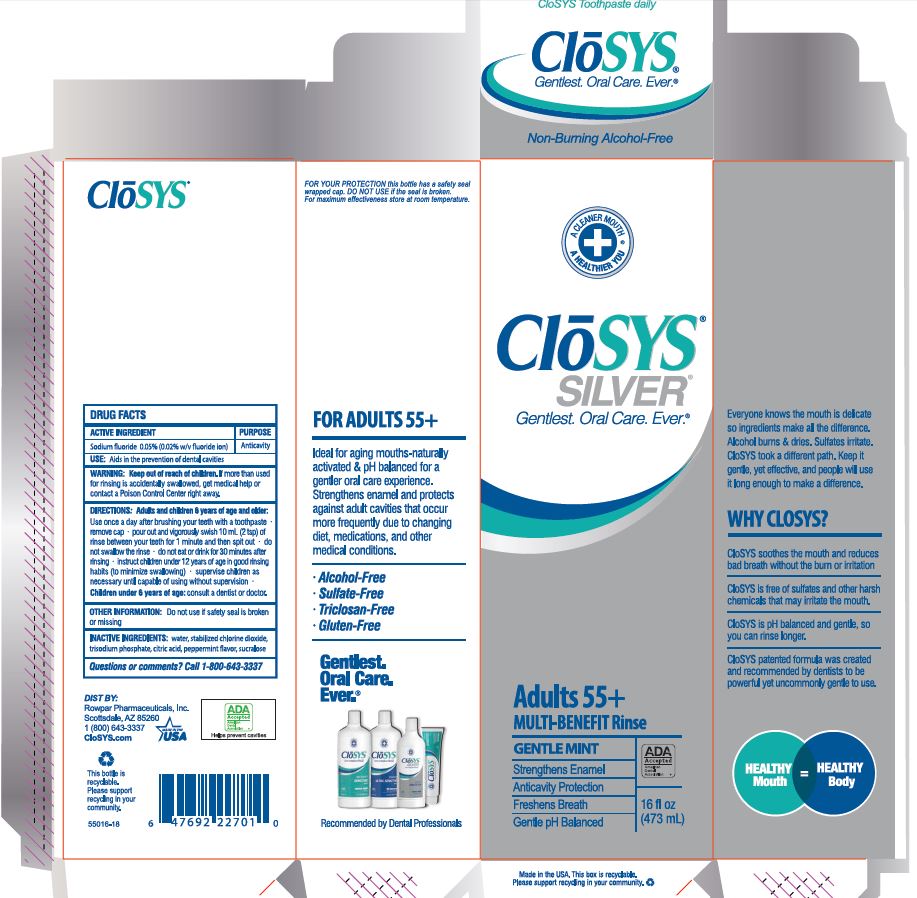 DRUG LABEL: CloSYS
NDC: 58578-1234 | Form: RINSE
Manufacturer: Rowpar Pharmaceuticals, Inc.
Category: otc | Type: HUMAN OTC DRUG LABEL
Date: 20251223

ACTIVE INGREDIENTS: SODIUM FLUORIDE 0.05 g/100 mL
INACTIVE INGREDIENTS: WATER; CHLORINE DIOXIDE; SODIUM PHOSPHATE, TRIBASIC, DODECAHYDRATE; ANHYDROUS CITRIC ACID; PEPPERMINT; SUCRALOSE

ClōSYS® Silver® ANTICAVITY FLUORIDE RINSE

ACTIVE INGREDIENT

Sodium fluoride 0.05% (0.02% w/v fluoride ion)

PURPOSE

Anticavity

USE:

Aids in the prevention of dental cavities

Keep out of reach of children. If more than used for rinsing is accidentally swallowed, get medical help or contact a Poison Control Center right away.

DIRECTIONS: Adults and children 6 years of age and older:

Use once a day after brushing your teeth with a toothpaste · remove cap · pour out and vigorously swish 10 ml (2 tsp) of rinse between your teeth for 1 minute and then spit out · do not swallow the rinse · do not eat or drink for 30 minutes after rinsing • instruct children under 12 years of age in good rinsing habits (to minimize swallowing) · supervise children as necessary until capable of using without supervision ·
Children under 6 years of age: consult a dentist or doctor.

OTHER INFORMATION:

Do not use if safety seal is broken or missing

INACTIVE INGREDIENTS:

water, stabilized chlorine dioxide, trisodium phosphate, citric acid, peppermint flavor, sucralose

Questions or comments? Call 1-800-643-3337

Packaging

473ml Inner Label

473 mL Carton

100 ml Label